DRUG LABEL: Sterile Cord Blood Collection Unit
NDC: 62646-791 | Form: SOLUTION
Manufacturer: Medsep Corporation
Category: prescription | Type: HUMAN PRESCRIPTION DRUG LABEL
Date: 20110309

ACTIVE INGREDIENTS: SODIUM CITRATE 0.921 g/35 mL; DEXTROSE MONOHYDRATE 0.893 g/35 mL; CITRIC ACID 0.114 g/35 mL; SODIUM PHOSPHATE, MONOBASIC, MONOHYDRATE 0.078 g/35 mL
INACTIVE INGREDIENTS: WATER

Sterile Cord Blood Collection Unit
Code 791-08

ANTICOAGULANT CITRATE PHOSPHATE DEXTROSE SOLUTION (CPD)

Sterile, non-pyrogenic fluid path. Sterilized by steam.

Rx only.

This product is free of natural rubber latex.

INDICATIONS AND USAGE

For collection of up to 210 ml of umbilical cord blood. Use aseptic technique.

Sterile Exterior

Contents inside overwrap pouch, within the foil envelope, are sterile and acceptable for use in a sterile field if pouch is unopened and undamaged; visual inspection to confirm the integrity of overwrap pouch should be performed.

WARNINGS

Do not irradiate collected cord blood or components.

Making multiple punctures of the umbilical cord to increase collection volume may increase the risk of contamination.

GENERAL PRECAUTIONS

Do not use if the package is damaged or seal is incomplete. Use only if solution is clear.

Sealing should be done in a manner that avoids fluid splatter.

Always dispose of blood-contaminated products in a manner consistent with established BIOHAZARD safety procedures.

HOW SUPPLIED

The Collection Unit inside the overwrap pouch, within the foil envelope, are sterile and acceptable for use in a sterile field if pouch is unopened and undamaged.

INFORMATION FOR PATIENTS

Medsep Corporation, A Subsidiary of Pall Corp., Covina, CA 91722, USA

Visit us at www.pall.com/medical

For Pall customer service, call: 1.800.645.6578

DonorCare is a registered trademark of ITL Corporation, Canberra, Australia. Produced under license from ThermoGenesis Corp.

Instructions for Use

1. Ensure DonorCare® Needle Guard (DCNG) is positioned on the tubing between the needle hub and Pinch Clamp. Engage Pinch Clamp. Ensure tethered cap is placed securely on the air vent.

2. Using aseptic technique, insert needle into umbilical vein, disengage Pinch Clamp to collect cord blood, mixing frequently, according to standard procedures.

3. Upon completion of collection, engage Pinch Clamp then withdraw needle from umbilical vein. Slide the DCNG midway over the needle hub. While holding the sides of DCNG near front, grasp tubing and pull smoothly, pulling needle into the DCNG until it locks into place. Confirm that needle is locked by listening for the second click as the needle is drawn into the DCNG. Ensure that tubing cannot be pulled through DCNG.

4. Place the bag on a work surface. While holding the tubing above the bag, open the tethered cap on the air vent. Allow the blood to drain from the tubing into the bag.

5. When the tubing has been drained, hold tubing vertical and seal tubing directly below the Y-piece with air vent.

6. Detach and discard needle, DCNG, Pinch Clamp, Air Vent and tubing according to standard procedures.

7. Determine amount of anticoagulated blood collected. If required, add sedimenting agent to CPD anticoagulated blood through Sample Port using a syringe according to standard procedures.

8. Mix well. Take care to strip and mix any blood in tubing.

9. Load bag into centrifuge cup. It is suggested that a means of support is used to prevent bag from collapsing and to reduce wrinkles.

10. Centrifuge according to standard procedures to obtain mononuclear cell-rich plasma.

BAG LABEL

Collection Bag Label

HPC, Cord Blood

ANTICOAGULANT CITRATE PHOSPHATE DEXTROSE SOLUTION

35 ml Anticoagulant Citrate Phosphate Dextrose Solution for collection of up to 210 ml of umbilical cord blood. Each 35 ml of CPD solution contains 0.921 g sodium citrate (dihydrate), USP; 0.893 g dextrose (monohydrate), USP; 0.114 g citric acid (monohydrate), USP; and 0.078 g monobasic sodium phosphate (monohydrate), USP. Use only if solution is clear.

Warning: This product may transmit infectious agents. Sterile, nonpyrogenic fluid path. Do not irradiate. Rx only.

Code 791-08

PATIENT COUNSELING INFORMATION

Issued August 2010, 147791082